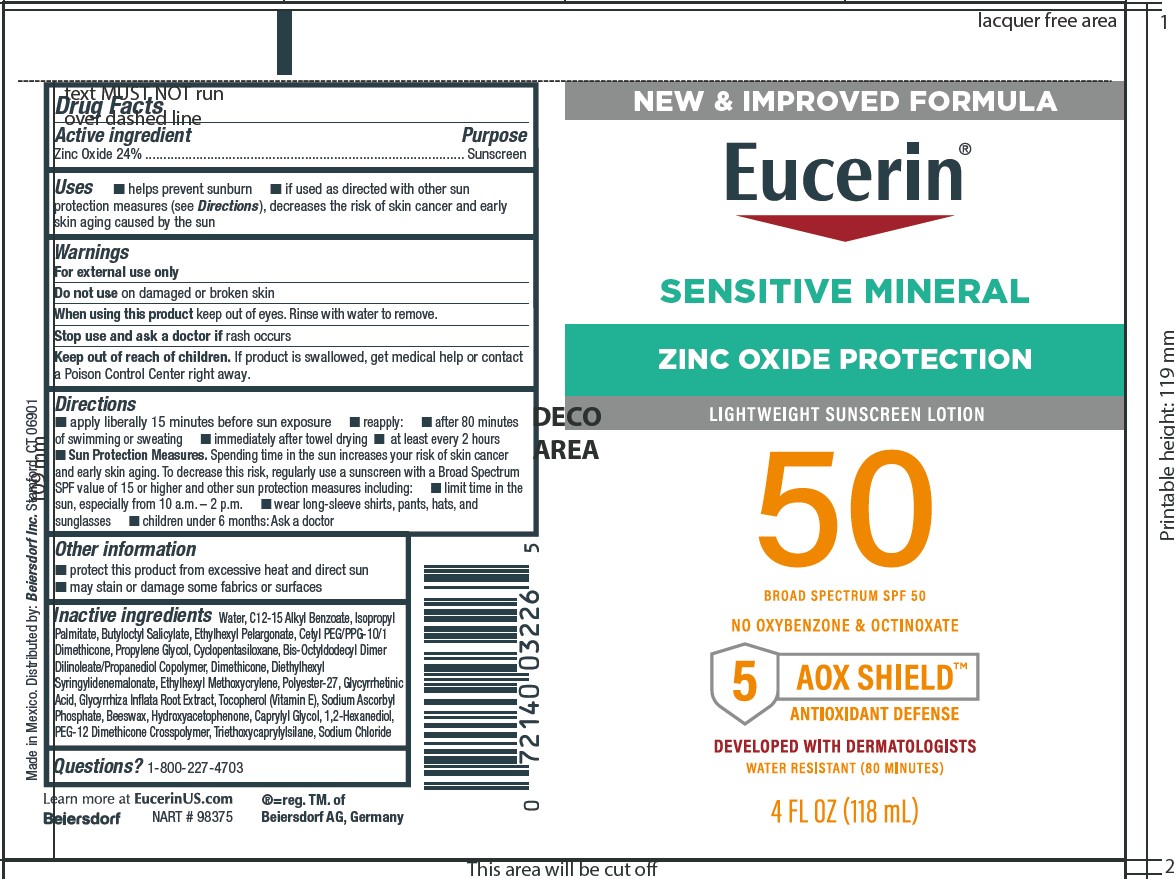 DRUG LABEL: Eucerin Sensitive Mineral SPF 50 Sunscreen
NDC: 66800-1000 | Form: LOTION
Manufacturer: Beiersdorf Inc
Category: otc | Type: HUMAN OTC DRUG LABEL
Date: 20251110

ACTIVE INGREDIENTS: ZINC OXIDE 24 g/100 g
INACTIVE INGREDIENTS: 1,2-HEXANEDIOL; TOCOPHEROL; PROPYLENE GLYCOL; POLYESTER-7; HYDROXYACETOPHENONE; CETYL PEG/PPG-10/1 DIMETHICONE (HLB 2); CYCLOMETHICONE 5; DIMETHICONE; SODIUM CHLORIDE; SYNTHETIC BEESWAX; BIS-OCTYLDODECYL DIMER DILINOLEATE/PROPANEDIOL COPOLYMER; ETHYLHEXYL METHOXYCRYLENE; TRIETHOXYCAPRYLYLSILANE; CAPRYLYL GLYCOL; WATER; ALKYL (C12-15) BENZOATE; ISOPROPYL PALMITATE; BUTYLOCTYL SALICYLATE; ETHYLHEXYL PELARGONATE; GLYCYRRHIZA INFLATA ROOT; GLYCYRRHETINIC ACID; SODIUM ASCORBYL PHOSPHATE; DIETHYLHEXYL SYRINGYLIDENEMALONATE

Eucerin Sensitive Mineral SPF 50 Sunscreen Lotion

Active ingredient

Zinc Oxide

Purpose

Sunscreen

Uses

■ helps prevent sunburn

■ if used as directed with other sun protection measures (see Directions), decreases the risk of skin cancer and early skin aging caused by the sun

Warnings

For external use only

Do not useon damaged or broken skin

WHEN USING

When using this productkeep out of eyes. Rinse with water to remove.

Stop use and ask a doctor ifrash occures

Keep out of reach of children.If product is swallowed, get medical help or contact a Poison Control Center right away.

Directions

■ apply liberally 15 minutes before sun exposure

■ reapply:

■ after 80 minutes of swimming or sweating

■ immediately after towel drying

■ at least every 2 hours

■ Sun Protection Measures.Spending time in the sun increases your risk of skin cancer and early skin aging. To decrease this risk, regularly use a sunscreen with a Broad Spectrum SPF value of 15 or higher and other sun protection measures including:

■ limit time in the sun, especially from 10 a.m. – 2 p.m.

■ wear long-sleeve shirts, pants, hats, and sunglasses

■ children under 6 months: Ask a doctor

Other information

■ protect this product from excessive heat and direct sun

■ may stain or damage some fabrics or surfaces

Inactive ingredients

Water, C12-15 Alkyl Benzoate, Isopropyl Palmitate, Butyloctyl Salicylate, Ethylhexyl Pelargonate, Cetyl PEG/PPG-10/1
Dimethicone, Propylene Glycol, Cyclopentasiloxane, Bis-Octyldodecyl Dimer Dilinoleate/Propanediol Copolymer, Dimethicone, Diethylhexyl Syringylidenemalonate, Ethylhexyl Methoxycrylene, Polyester-27, Glycyrrhetinic Acid, Glycyrrhiza Inflata Root Extract, Tocopherol (Vitamin E), Sodium Ascorbyl Phosphate, Beeswax, Hydroxyacetophenone, Caprylyl Glycol, 1,2-Hexanediol,
PEG-12 Dimethicone Crosspolymer, Triethoxycaprylylsilane, Sodium Chloride

Questions?

1-800-227-4703

PACKAGE LABEL

Eucerin®

Sensitive Mineral

Zinc Oxide Protection

Lightweight Sunscreen Lotion

50 Broad Spectrum SPF 50

Hypoallergenic | Fragrance Free

No Oxybenzone and Octinoxate

5 AOX Shield Antioxidant Defense

Developed With Dermatologists

Water Resistant (80 Minutes)

4 FL OZ (118 mL)